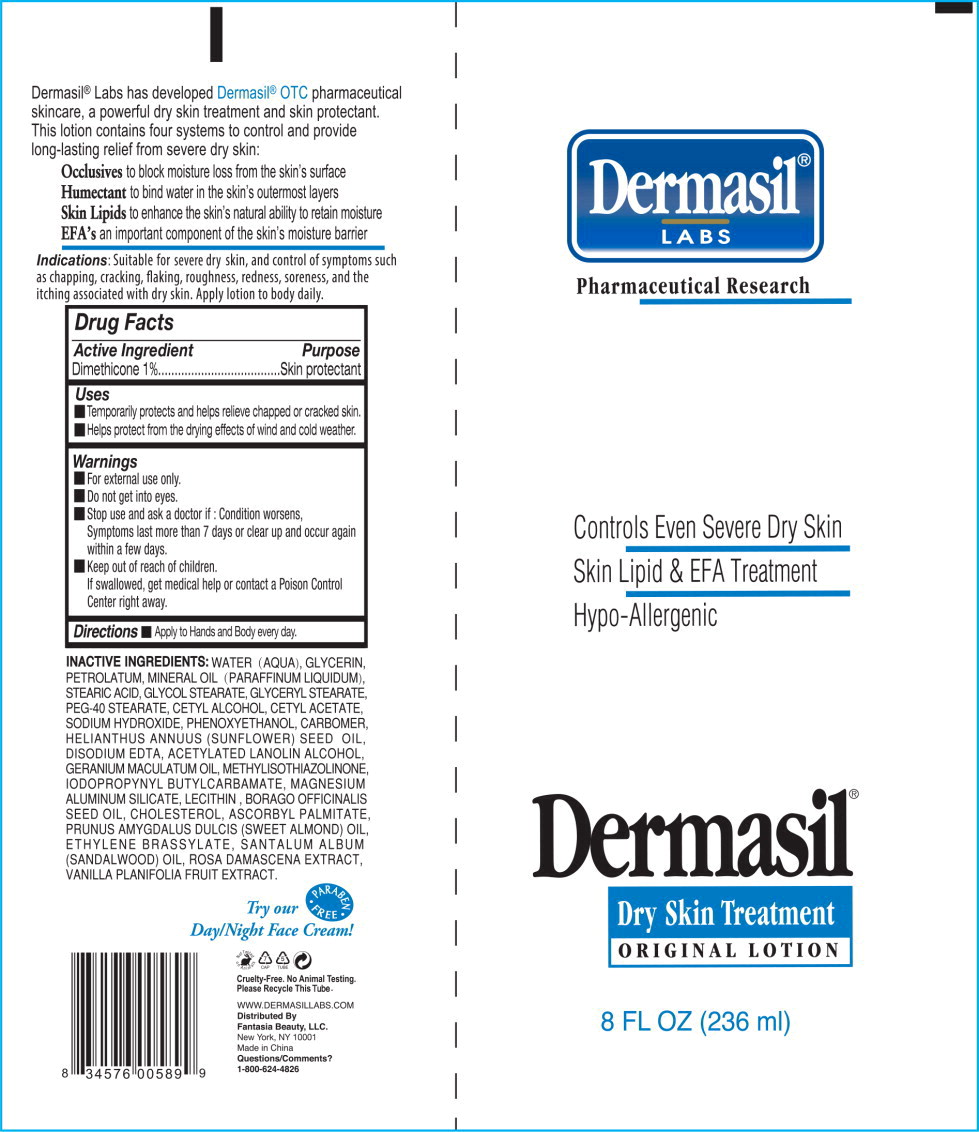 DRUG LABEL: DERMASIL DRYSKIN
NDC: 76184-0101 | Form: LOTION
Manufacturer: Fantasia Beauty LLC
Category: otc | Type: HUMAN OTC DRUG LABEL
Date: 20250218

ACTIVE INGREDIENTS: DIMETHICONE 0.01 g/1 mL
INACTIVE INGREDIENTS: WATER; GLYCERIN; PETROLATUM; MINERAL OIL; STEARIC ACID; GLYCOL STEARATE; GLYCERYL MONOSTEARATE; PEG-40 MONOSTEARATE; CETYL ALCOHOL; CETYL OLEATE; SODIUM HYDROXIDE; PHENOXYETHANOL; CARBOMER HOMOPOLYMER TYPE C; SUNFLOWER OIL; EDETATE DISODIUM; ACETYLATED LANOLIN ALCOHOLS; GERANIUM MACULATUM ROOT OIL; METHYLISOTHIAZOLINONE; IODOPROPYNYL BUTYLCARBAMATE; MAGNESIUM ALUMINUM SILICATE; LECITHIN, SOYBEAN; BORAGE OIL; CHOLESTEROL; ASCORBYL PALMITATE; ALMOND OIL; ETHYLENE BRASSYLATE; SANDALWOOD OIL; ROSA DAMASCENA FLOWER; VANILLA

Drug Facts

Active Ingredient

Dimethicone 1%

Purpose

Skin protectant

Uses

- Temporarily protects and helps relieve chapped or cracked skin.
- Helps protect from the drying effects of wind and cold weather.

Warnings

- For external use only.
- Do not get into eyes.

- Stop use and ask a doctor if: Condition worsens, Symptoms last more than 7 days or clear up and occur again within a few days.

- Keep out of reach of children.
  If swallowed, get medical help or contact a Poison Control Center right away.

Directions

- Apply to Hands and Body every day.

INACTIVE INGREDIENTS:

WATER (AQUA), GLYCERIN, PETROLATUM, MINERAL OIL (PARAFFINUM LIQUIDUM), STEARIC ACID, GLYCOL STEARATE, GLYCERYL STEARATE, PEG-40 STEARATE, CETYL ALCOHOL, CETYL ACETATE, SODIUM HYDROXIDE, PHENOXYETHANOL, CARBOMER, HELIANTHUS ANNUUS (SUNFLOWER) SEED OIL, DISODIUM EDTA, ACETYLATED LANOLIN ALCOHOL, GERANIUM MACULATUM OIL, METHYLISOTHIAZOLINONE, IODOPROPYNYL BUTYLCARBAMATE, MAGNESIUM ALUMINUM SILICATE, LECITHIN , BORAGO OFFICINALIS SEED OIL, CHOLESTEROL, ASCORBYL PALMITATE, PRUNUS AMYGDALUS DULCIS (SWEET ALMOND) OIL, ETHYLENE BRASSYLATE, SANTALUM ALBUM (SANDALWOOD) OIL, ROSA DAMASCENA EXTRACT, VANILLA PLANIFOLIA FRUIT EXTRACT.

Principal Display Panel - Dermasil Original 8 Tube Label

Dermasil®

LABS

Pharmaceutical Research

Controls Even Severe Dry Skin

Skin Lipid & EFA Treatment

Hypo-Allergenic

Dermasil®

Dry Skin Treatment

ORIGINAL LOTION

8 FL OZ (236 ml)